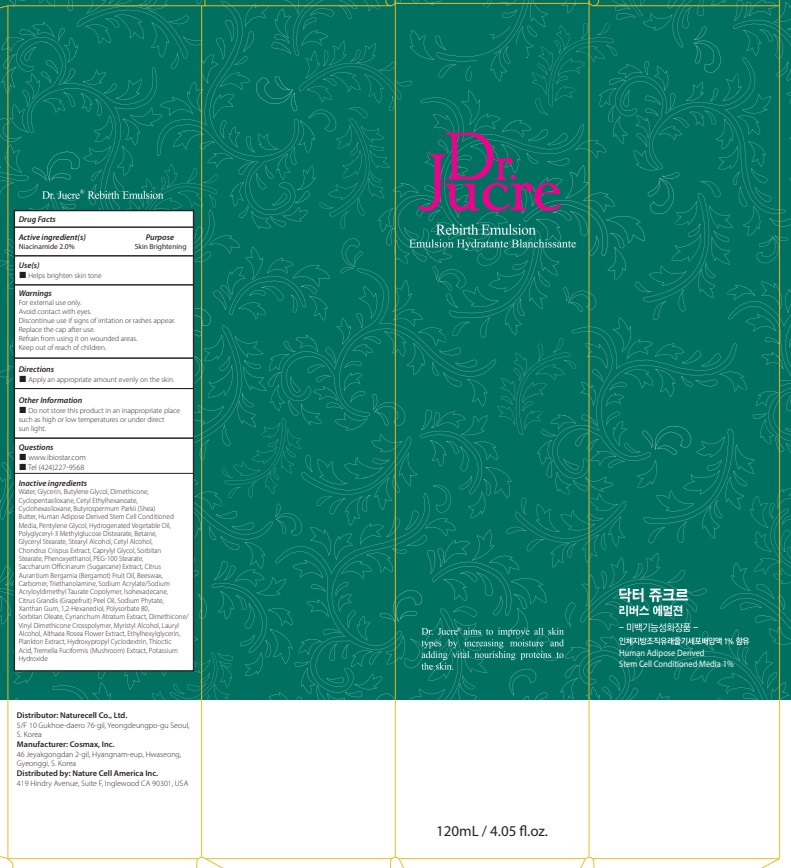 DRUG LABEL: Dr.Jucre Rebirth
NDC: 83071-140 | Form: EMULSION
Manufacturer: NATURECELL CO., LTD.
Category: otc | Type: HUMAN OTC DRUG LABEL
Date: 20250102

ACTIVE INGREDIENTS: NIACINAMIDE 2 g/100 mL
INACTIVE INGREDIENTS: WATER; GLYCERIN; BUTYLENE GLYCOL

ACTIVE INGREDIENTS

Niacinamide 2.0%

INACTIVE INGREDIENTS

Water, Glycerin, Butylene Glycol, Dimethicone, Cyclopentasiloxane, Cetyl Ethylhexanoate, Cyclohexasiloxane, Butyrospermum Parkii (Shea) Butter, Human Adipose Derived Stem Cell Conditioned Media, Pentylene Glycol, Hydrogenated Vegetable Oil, Polyglyceryl-3 Methylglucose Distearate, Betaine, Glyceryl Stearate, Stearyl Alcohol, Cetyl Alcohol, Chondrus Crispus Extract, Caprylyl Glycol, Sorbitan Stearate, Phenoxyethanol, PEG-100 Stearate, Saccharum Officinarum (Sugarcane) Extract, Citrus Aurantium Bergamia (Bergamot) Fruit Oil, Beeswax, Carbomer, Triethanolamine, Sodium Acrylate/Sodium Acryloyldimethyl Taurate Copolymer, Isohexadecane, Citrus Grandis (Grapefruit) Peel Oil, Sodium Phytate, Xanthan Gum, 1,2-Hexanediol, Polysorbate 80, Sorbitan Oleate, Cynanchum Atratum Extract, Dimethicone/Vinyl Dimethicone Crosspolymer, Myristyl Alcohol, Lauryl Alcohol, Althaea Rosea Flower Extract, Ethylhexylglycerin, Plankton Extract, Hydroxypropyl Cyclodextrin, Thioctic Acid, Tremella Fuciformis (Mushroom) Extract, Potassium Hydroxide

PURPOSE

Skin Brightening

WARNINGS

For external use only.
Avoid contact with eyes.
Discontinue use if signs of irritation or rashes appear.
Replace the cap after use.
Refrain from using it on wounded areas.
Keep out of reach of children.

KEEP OUT OF REACH OF CHILDREN

Keep out of the reach of children.

Uses

■ Helps brighten skin tone

Directions

■ Apply an appropriate amount evenly on the skin.

Other Information

■ Do not store this product in an inappropriate place such as high or low temperatures or under direct sun light.

Questions

■ www.ibiostar.com
■ Tel (424)227-9568